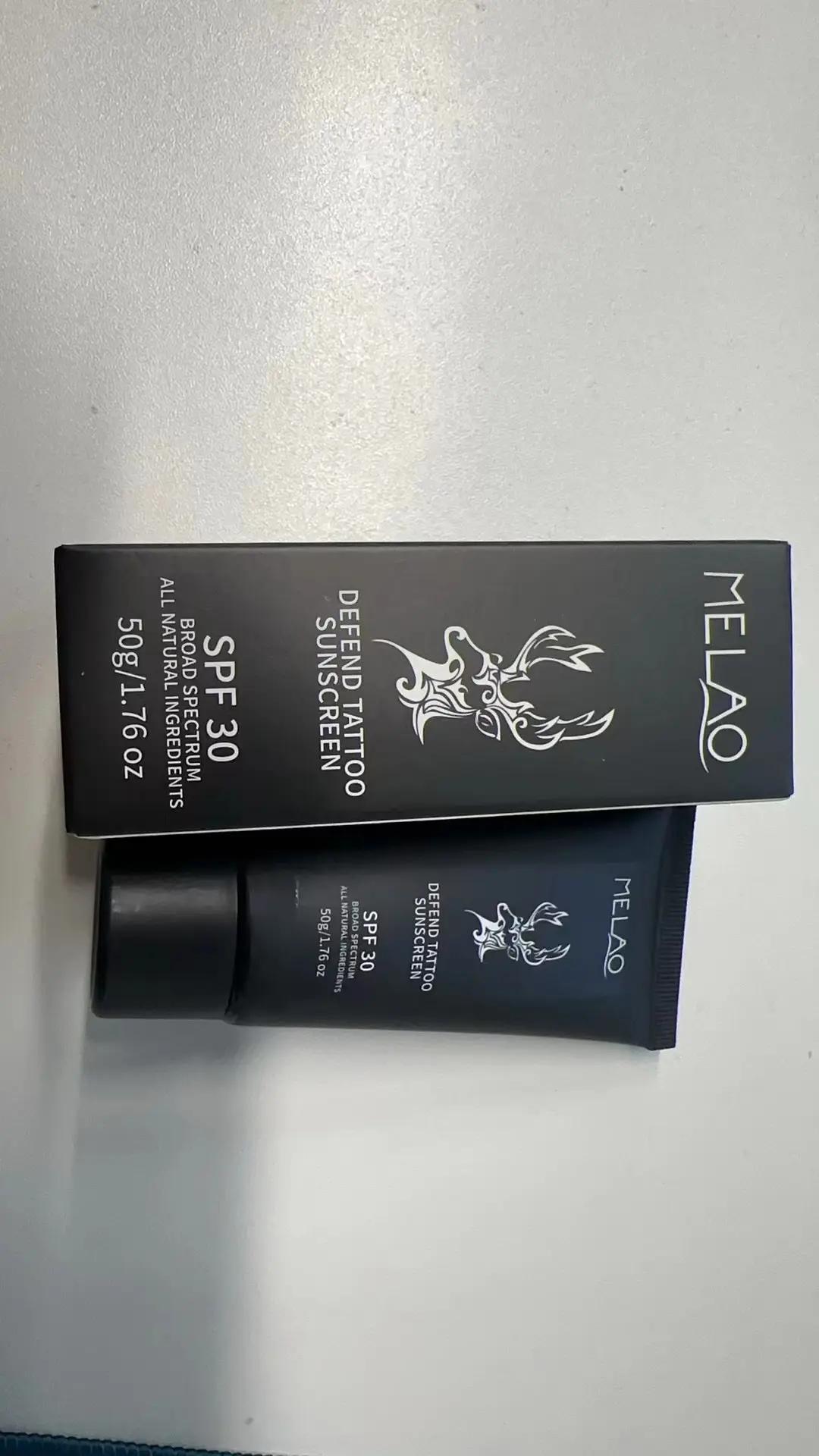 DRUG LABEL: MELAO Defend Tattoo Sunscreen
NDC: 83566-575 | Form: LIQUID
Manufacturer: Guangzhou Yilong Cosmetics Co., Ltd
Category: otc | Type: HUMAN OTC DRUG LABEL
Date: 20240808

ACTIVE INGREDIENTS: ALUMINUM CHLOROHYDREX PROPYLENE GLYCOL 3 g/100 g
INACTIVE INGREDIENTS: NIACINAMIDE 3 g/100 g; GLYCERIN 3 g/100 g; ALLANTOIN 2 g/100 g; TITANIUM DIOXIDE 3 g/100 g; WATER O-15 52 g/100 g; ASCORBIC ACID 4 g/100 g; ZINC OXIDE 3 g/100 g; CETEARYL BEHENATE 1.5 g/100 g; TREHALOSE 3 g/100 g

MELAO Defend Tattoo Sunscreen

-Active ingredients

Propylene Glycol 3%

Cetearyl Alcohol 1.5%

Inactive ingredients

Water 52%
Ascorbic Acid 4%
Titanium Dioxide 3%
Zinc Oxide 3%
Niacinamide 3%
Glycerin 3%
Trehalose 3%
Allantoin 2%
Sodium Hyaluronate 2%
Dipotassium Glycyrrhizate 2%
Limnanthes Alba (Meadowfoam) Seed Oil 2%
Macadamia Ternifolia Seed Oil 2%
Triticum Vulgare (Wheat) Germ Oil 2%
Ethylhexyl Salicylate 1.8%
C12-15 Alkyl Benzoate 1.5%
Cetearyl Glucoside 1.5%
Ceteareth-2 1.4%
Dimethicone 1.4%
Menthol 1%
Tocopheryl Acetate 0.7%
Bisabolol 0.5%
Xanthan Gum 0.5%
Ethylhexylglycerin 0.5%
Chlorphenesin 0.5%
Mentha Arvensis Extract 0.4%
Paeonia Albiflora Root Extract 0.2%
Triticum Vulgare (WheatGerm Extract 0.2%
Centella Asiatica Root Extract 0.15%
Aloe Barbadensis Leaf Extract 0.15%
Parfum 0.1%

Purpose

Sunscreen

Uses

Step 1: Clean and thoroughly dry your skin.

Step 2: Squeeze out an appropriate amount of sunscreen.

Step 3: Gently apply to the surface of the skin.

Warning

For external use only.

Stop use and ask a doctor if

rash occurs.

Do not use

on damaged or broken skin.

When using this product

keep out of eyes. Rinse withwater to remove.

Keep out of reach of children.

If swallowed, get medical help or contact a Poison Control Center right away.

DOSAGE & ADMINISTRATION

Squeeze out an appropriate amount of sunscreen and spread evenly on skin.